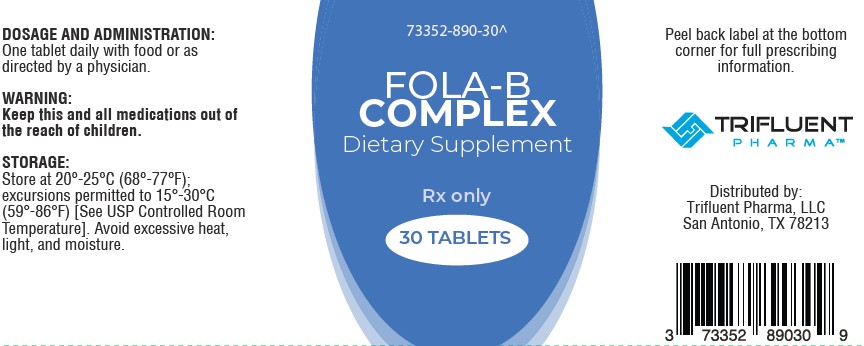 DRUG LABEL: Fola-B Complex
NDC: 73352-890 | Form: TABLET
Manufacturer: Trifluent Pharma LLC
Category: other | Type: DIETARY SUPPLEMENT
Date: 20250722

ACTIVE INGREDIENTS: PYRIDOXINE HYDROCHLORIDE 10 mg/1 1; FOLIC ACID 1000 ug/1 1; CYANOCOBALAMIN 400 ug/1 1
INACTIVE INGREDIENTS: CALCIUM PHOSPHATE; STEARIC ACID; CROSCARMELLOSE SODIUM; MAGNESIUM STEARATE; SILICON DIOXIDE; TRIACETIN; POLYDEXTROSE; HYDROXYPROPYL CELLULOSE, UNSPECIFIED; CARNAUBA WAX

FOLA-B COMPLEX
Dietary Supplement

HEALTH CLAIM

FOLA-B COMPLEX - Rx only [Dispensed by Prescription]
Prescription only Folic Acid Containing Dietary Supplement

STATEMENT OF IDENTITY

FOLA-B COMPLEX
ACTIVE INGREDIENTS: Each tablet contains pyridoxine hydrochloride, folic acid, cyanocobalamin.

Serving Size: 1 Tablet; Serving per Container: 30
Each Tablet Contains: |  | % Daily Value
Vitamin B-6 (as Pyridoxine HCl) | 10 mg | 588%
Folate | 1,667 mcg DFE; (from 1,000 mcg Folic Acid) | 417%
Vitamin B-12; (as Cyanocobalamin) | 400 mcg | 16,667%

OTHER INGREDIENTS: Calcium Phosphate, Modified Cellulose, Stearic Acid, Croscarmellose Sodium, Magnesium Stearate, Silicon Dioxide, Triacetin, Polydextrose, Wax.

DESCRIPTION

FOLA-B COMPLEX is an orally administered prescription only dietary supplement.

INDICATIONS

FOLA-B COMPLEXTM tablets are indicated for nutritional support and folic acid supplementation.*

CONTRADINDICATIONS

FOLA-B COMPLEX is contraindicated in patients with a known hypersensitivity to any of the ingredients.

WARNING

Keep this and all medications out of the reach of children.

Folic acid alone is improper therapy in the treatment of pernicious anemia and other megaloblastic anemias where Vitamin B12 is deficient.

ADVERSE REACTIONS

Allergic sensitization has been reported following both oral and parenteral administration of folic acid.

You should call your doctor for medical advice about serious adverse events. To report adverse side effects or to obtain product information, contact: Trifluent Pharma, LLC at 1-210-944-6920.

DOSAGE AND ADMINISTRATION

One tablet daily with food or as directed by a physician.

Before, during and/or after pregnancy, one tablet daily with food or as directed by a physician.

PRECAUTION:

Folic acid in doses as low as 0.1 mg daily may obscure pernicious anemia in that hematologic remission can occur while neurologic manifestations remain progressive.

STORAGE

Store at 20°-25°C (68°-77°F) excursions permitted to 15°-30°C (59°-86°F) [See USP Controlled Room Temperature.]

Avoid excessive heat, light and moisture.

How Supplied

Fola-B Complex, 30 Tablets in a bottle, 73352-890-30^

Tablet is pink, round.

Distributed by:
Trifluent Pharma, LLC,
San Antonio TX

Rev 01 890-30

TAMPER EVIDENT Double safety sealed for your protection. Do not use if either
seal is broken or missing.

MADE IN USA

*This statement has not been evaluated by the Food and Drug
Administration. This product is not intended to diagnose, treat, cure,
or prevent any disease.

^Trifluent Pharma does not represent this product code to be National Drug Code (NDC). Product
codes are formatted according to standard industry practice to meet the formatting requirement by
pedigree reporting and supply-chain control including pharmacies.

This product is a prescription-folate with or without other dietary ingredients that – due
to increased folate levels increased risk associated with masking B12 deficiency
(pernicious anemia) requires administration under the care of a licensed
medical practitioner. The most appropriate way to ensure pedigree reporting
consistent with these regulatory guidelines and safety monitoring is to dispense this
product only by prescription. This is not an Orange Book product. This product may be
administered only under a physician's supervision and all prescriptions using this
product shall be pursuant to state statues as applicable. The ingredients, indication,
or claims of this product are not to be construed to be drug claims.
1. Federal Register Notice of
August 2, 1973 (38 FR 20750)
2. Federal Register Notice of
October 17, 1980 (45 FR
69043, 69044)
3. Federal Register Notice of
April 9, 1971 (36 FR 6843)